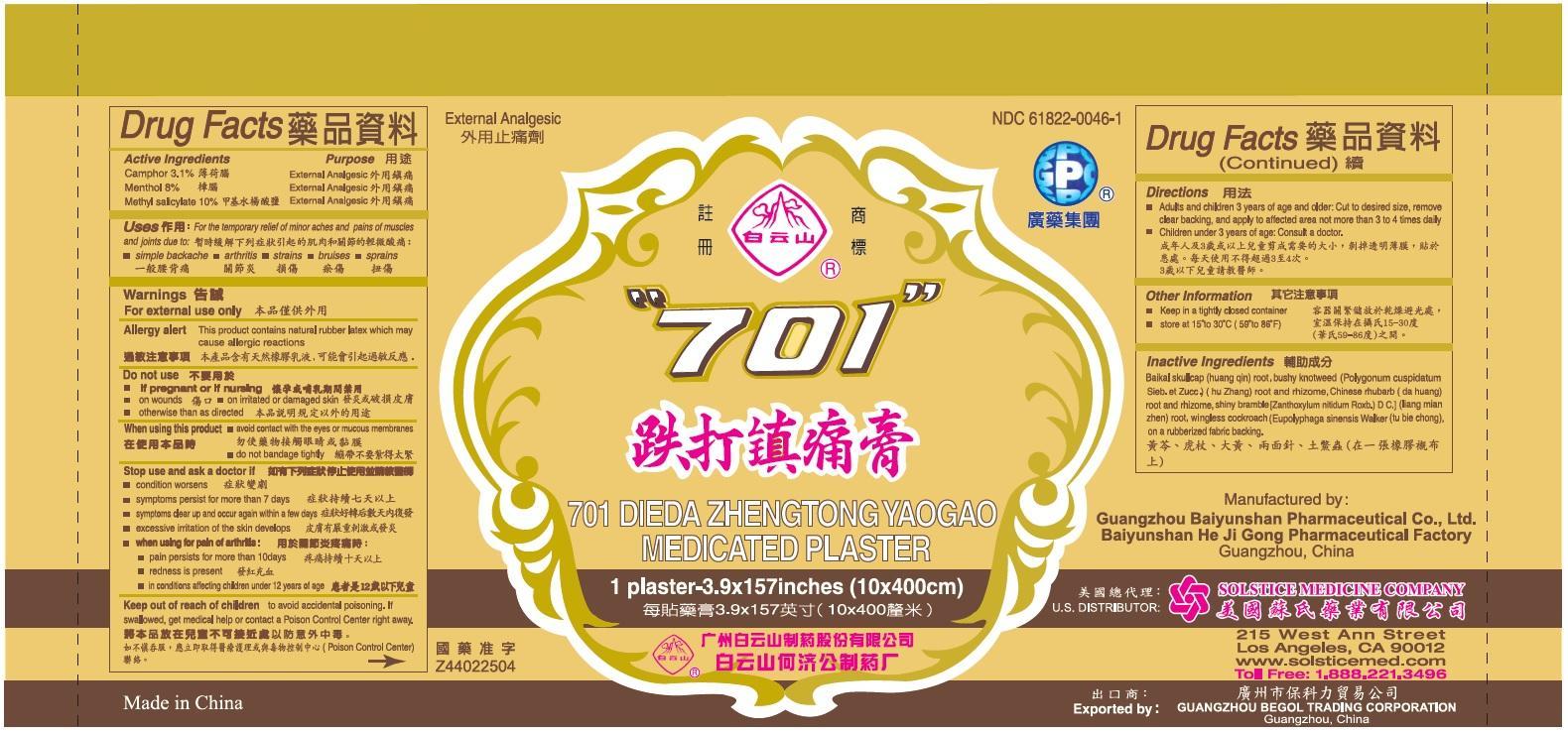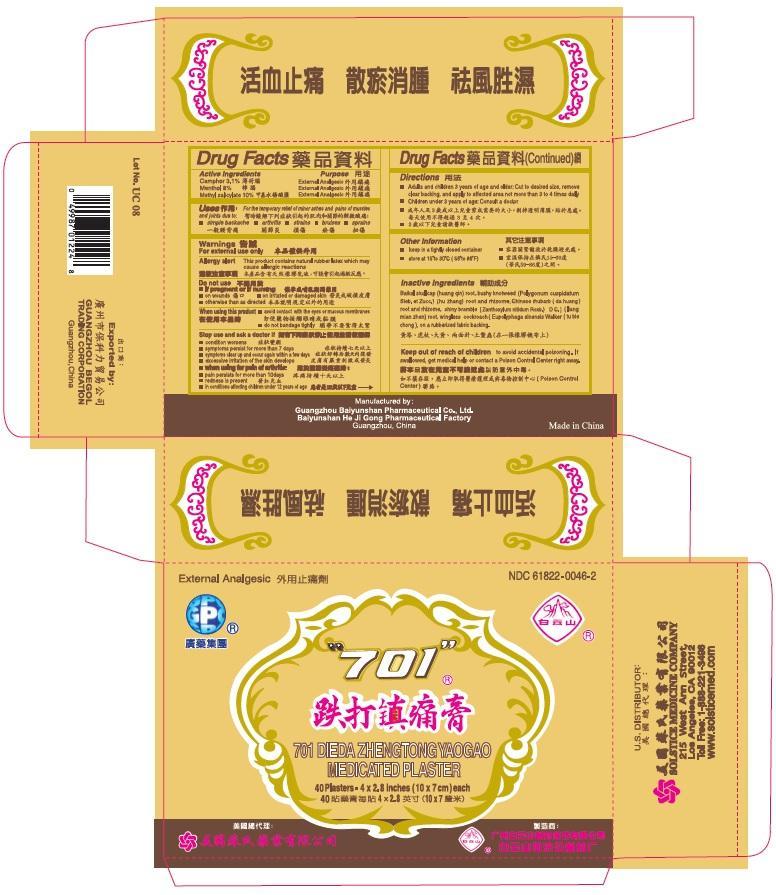 DRUG LABEL: 701 DIEDA ZHENGTONG YAOGAO MEDICATED
NDC: 61822-0046 | Form: PLASTER
Manufacturer: GUANGZHOU BAIYUNSHAN PHARMACEUTICAL CO., LTD. BAIYUNSHAN HEJIGONG PHARMACEUTICAL FACTORY
Category: otc | Type: HUMAN OTC DRUG LABEL
Date: 20191113

ACTIVE INGREDIENTS: CAMPHOR (SYNTHETIC) 3.1 g/1 1; MENTHOL 8 g/1 1; METHYL SALICYLATE 10 g/1 1
INACTIVE INGREDIENTS: SCUTELLARIA BAICALENSIS ROOT; POLYGONUM CUSPIDATUM WHOLE; RHEUM TANGUTICUM WHOLE; ZANTHOXYLUM NITIDUM ROOT; EUPOLYPHAGA SINENSIS

Drug Facts

Active ingredients
Camphor 3.1%
Menthol 8%
Methyl salicylate 10%

Purpose
External analgesic
External analgesic
External analgesic

Uses
For the temporary relief of minor aches and pains of muscles and joints due to:
simple backache
arthritis
strains
bruises
sprains

Warnings
For external use only
Allergy alert: This product contains natural rubber latex which may cause allergic reactions

Do not use
on irritated or damaged skin
on wounds
with a heating pad
if pregnant or nursing
otherwise than as directed

When using this product
avoid contact with the eyes or mucous membranes
do not bandage tightly

Stop use and ask a doctor if
condition worsens
symptoms persist for more than 7 days
symptoms clear up and occur again within a few days
excessive irritation of the skin develops
nausea, vomiting, abdominal discomfort, diarrhea, or skin rash occurs
when using for pain of arthritis:
pain persists for more than 10 days
redness is present
in conditions affecting children under 12 years of age

Keep out of reach of children to avoid accidental poisoning.
If swallowed, get medical help or contact a Poison Control Center right away.

Directions
Clean the affected area. Remove the paper film from the plaster.
adults and children 12 years of age and older: apply one plaster to affected area not more than 3 to 4 times daily
children under 12 years of age: do not use, consult your physician refer to the above warnings; use otherwise than as directed may be dangerous

Other information
keep in a tightly closed container
store at room temperature 15º to 30º C (59º to 86º F), away from sunlight

Inactive ingredients
baikal skullcap (huang qin) root, bushy knotweed (polygonum cuspidatum sieb. et zucc.) (hu zhang) root and rhizome, Chinese rhubarb (da huang) root and rhizome, shiny bramble (zanthoxylum nitidum roxb.) D C (liang mian zhen) root, wingless cockroach (eupolyphaga sinenesis walker) (tu bie chong), on a rubberized fabric backing.

PACKAGE LABEL

701 DIEDA ZHENGTONG YAOGAO MEDICATED PLASTER

NDC 61822-0046-1

External Analgesic

1 Plaster – 3.9 x 157 inches (10 x 400 cm)

701 DIEDA ZHENGTONG YAOGAO MEDICATED PLASTER

NDC 61822-0046-2

External Analgesic

10 Plasters – 4 x 2.8 inches (10 x 7 cm) each